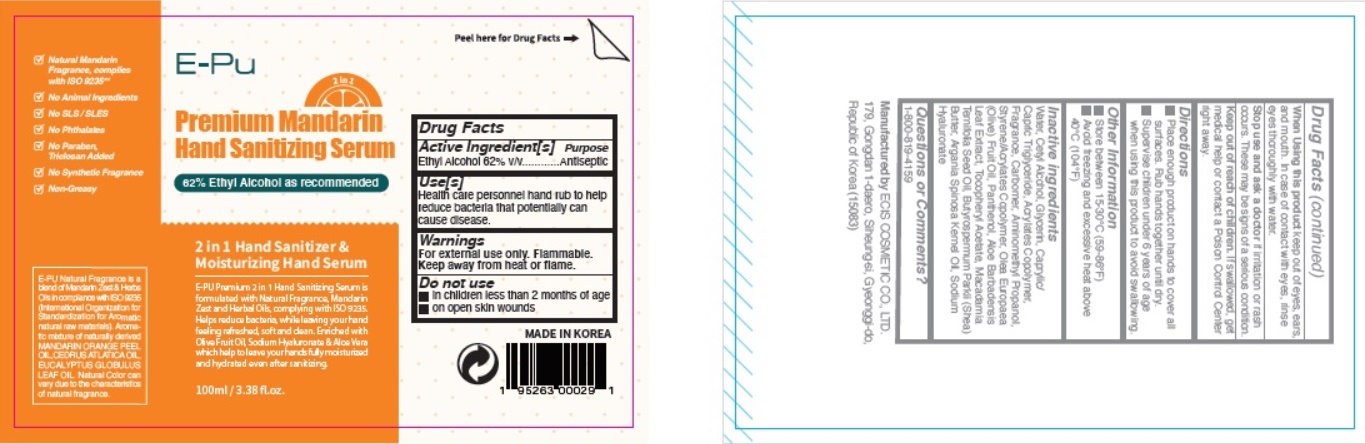 DRUG LABEL: E-PU Premium Mandarin Hand Sanitizing Serum
NDC: 73862-218 | Form: LOTION
Manufacturer: E.CIS Cosmetic Co.,Ltd
Category: otc | Type: HUMAN OTC DRUG LABEL
Date: 20200624

ACTIVE INGREDIENTS: ALCOHOL 62 mL/100 mL
INACTIVE INGREDIENTS: BUTYL ACRYLATE/METHYL METHACRYLATE/METHACRYLIC ACID COPOLYMER (18000 MW); ALOE VERA LEAF; ARGAN OIL; HYALURONATE SODIUM; ACRYLIC ACID; GLYCERIN; CETYL ALCOHOL; WATER; MEDIUM-CHAIN TRIGLYCERIDES; .ALPHA.-TOCOPHEROL ACETATE; CARBOMER 940; MACADAMIA OIL; AMINOMETHYLPROPANOL; OLIVE OIL; PANTHENOL; SHEA BUTTER

E-PU Premium Mandarin Hand Sanitizing Serum

Active Ingredient(s)

Alcohol 62% v/v. Purpose: Antiseptic

Purpose

Antiseptic

Use

Health care personnel hand rub to help reduce bacteria that potentially can cause disease.

Warnings

For external use only. Flammable. Keep away from heat or flame

Do not use

- in children less than 2 months of age
- on open skin wounds

When using this product keep out of eyes, ears, and mouth. In case of contact with eyes, rinse eyes thoroughly with water.

Stop use and ask a doctor if irritation or rash occurs. These may be signs of a serious condition.

Keep out of reach of children. If swallowed, get medical help or contact a Poison Control Center right away.

Directions

- Place enough product on hands to cover all surfaces. Rub hands together until dry.
- Supervise children under 6 years of age when using this product to avoid swallowing.

Other information

- Store between 15-30C (59-86F)
- Avoid freezing and excessive heat above 40C (104F)

Inactive ingredients

Water, Cetyl Alcohol, Glycerin, Caprylic/Capric Triglyceride, Acrylates Copolymer, Fragrance, Carbomer, Aminomethyl Propanol, Styrene/Acrylates Copolymer, Olea Europaea (Olive) Fruit Oil, Panthenol, Aloe Barbadensis Leaf Extract, Tocopheryl Acetate, Macadamia Ternifolia Seed Oil, Butyrospermum Parkii (Shea) Butter, Argania Spinosa Kernel Oil, Sodium Hyaluronate

Package Label - Principal Display Panel

E-PU
2 in 1
Premium Mandarin
Hand Sanitizing Serum
62% Ethyl Alcohol as recommended
2 in 1 Hand Sanitizer & Moisturizing Hand Serum
E-PU Premium 2 in 1 Hand Sanitizing Serum is
formulated with Natural Fragrance, Mandarin
Zest and Herbal Oils, complying with ISO 9235.
Helps reduce bacteria, while leaving your hand
feeling refreshed, soft and clean. Enriched with
Olive Fruit Oil, Sodium Hyaluronate & Aloe Vera
which help to leave your hands fully moisturized
and hydrated even after sanitizing.
100ml / 3.38 fl.oz.